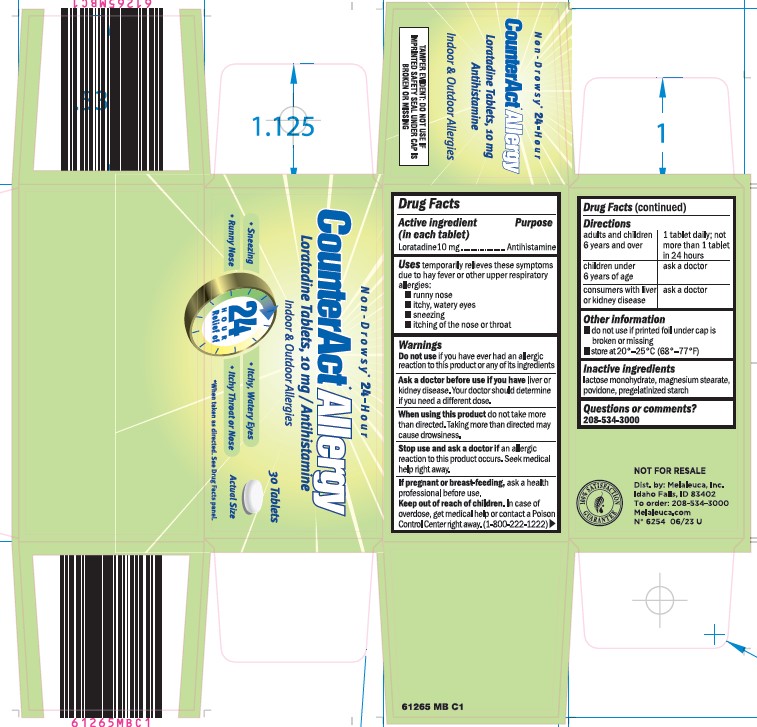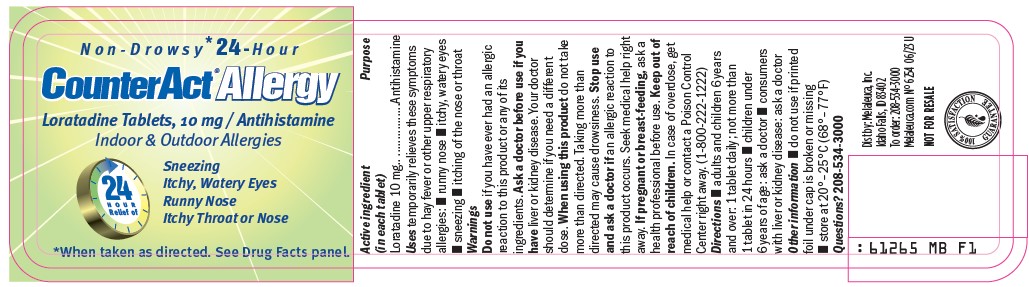 DRUG LABEL: CounterAct
NDC: 54473-166 | Form: TABLET
Manufacturer: Melaleuca, Inc.
Category: otc | Type: HUMAN OTC DRUG LABEL
Date: 20250317

ACTIVE INGREDIENTS: LORATADINE 10 mg/1 1
INACTIVE INGREDIENTS: LACTOSE MONOHYDRATE; MAGNESIUM STEARATE; POVIDONE; STARCH, CORN

CounterAct Allergy Content of Label

Active ingredient (in each tablet)
Loratadine 10 mg

Purpose
Antihistamine

INDICATIONS AND USAGE

Use temporarily relieves these symptoms due to hay fever or other upper respiratory allergies:

- runny nose
- itchy, watery eyes
- sneezing
- itching of the nose or throat

Warnings

Do not use if you have ever had an allergic reaction to this product or any of its ingredients

Ask a doctor before use if you have liver or kidney disease. Your doctor should determine if you need a different dose.

When using this product do not take more than directed. Taking more than directed may cause drowsiness.

Stop use and ask a doctor if an allergic reaction to this product occurs. Seek medical help right away.

PREGNANCY OR BREAST FEEDING

If pregnant or breast-feeding, ask a health processional before use.

Keep out of reach of children. In case of overdose, get medical help or contact a Poison Control Center right away.

Directions

adults and children 6 years and over |  | 1 tablet daily; not more than 1 tablet in 24 hours
children under 6 years of age |  | ask a doctor
consumers with liver or kidney disease |  | ask a doctor

Other information

- store at 20°-25°C (68°-77°F)
- protect from excessive moisture

INACTIVE INGREDIENT

Inactive ingredients lactose monohydrate, magnesium stearate, povidone, pregelatinized starch

Questions or comments? 1-800-282-3000